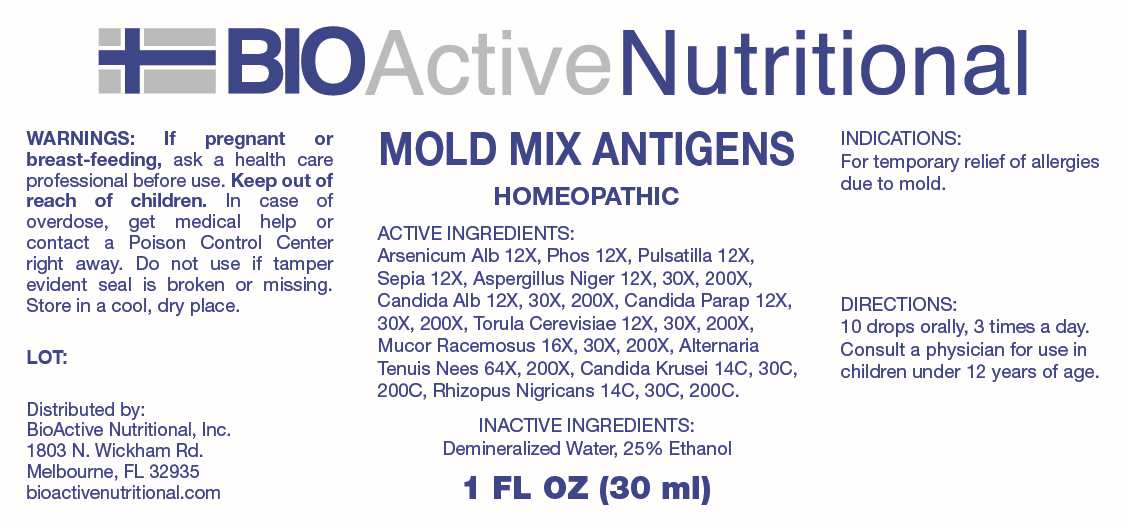 DRUG LABEL: Mold Mix Antigens
NDC: 43857-0649 | Form: LIQUID
Manufacturer: BioActive Nutritional, Inc.
Category: homeopathic | Type: HUMAN OTC DRUG LABEL
Date: 20241230

ACTIVE INGREDIENTS: ARSENIC TRIOXIDE 12 [hp_X]/1 mL; PHOSPHORUS 12 [hp_X]/1 mL; PULSATILLA PRATENSIS WHOLE 12 [hp_X]/1 mL; SEPIA OFFICINALIS JUICE 12 [hp_X]/1 mL; ASPERGILLUS NIGER VAR. NIGER 12 [hp_X]/1 mL; CANDIDA ALBICANS 12 [hp_X]/1 mL; CANDIDA PARAPSILOSIS 12 [hp_X]/1 mL; SACCHAROMYCES CEREVISIAE 12 [hp_X]/1 mL; MUCOR RACEMOSUS 16 [hp_X]/1 mL; ALTERNARIA ALTERNATA 64 [hp_X]/1 mL; ISSATCHENKIA ORIENTALIS WHOLE 14 [hp_C]/1 mL; RHIZOPUS STOLONIFER 14 [hp_C]/1 mL
INACTIVE INGREDIENTS: WATER; ALCOHOL

DRUG FACTS:

ACTIVE INGREDIENTS:

Arsenicum Album 12X, Phosphorus 12X, Pulsatilla 12X, Sepia 12X, Aspergillus Niger 12X, 30X, 200X, Candida Albicans 12X, 30X, 200X, Candida Parapsilosis 12X, 30X, 200X, Torula Cerevisiae 12X, 30X, 200X, Mucor Racemosus 16X, 30X, 200X, Alternaria Tenuis Nees 64X, 200X, Candida Krusei 14C, 30C, 200C, Rhizopus Nigricans 14C, 30C, 200C.

PURPOSE:

For temporary relief of allergies due to mold.

WARNINGS:

If pregnant or breast-feeding, ask a health care professional before use.

Keep out of reach of children. In case of overdose, get medical help or contact a Poison Control Center right away.

Do not use if tamper evident seal is broken or missing.

Store in a cool, dry place.

KEEP OUT OF REACH OF CHILDREN:

In case of overdose, get medical help or contact a Poison Control Center right away.

DIRECTIONS:

10 drops orally, 3 times a day. Consult a physician for use in children under 12 years of age.

INDICATIONS:

For temporary relief of allergies due to mold.

INACTIVE INGREDIENTS:

Demineralized Water, 25% Ethanol

QUESTIONS:

Distributed by:
BioActive Nutritional, Inc.
1803 N. Wickham Rd.
Melbourne, FL 32935
bioactivenutritional.com

PACKAGE LABEL DISPLAY:

BIOActiveNutritional

MOLD MIX ANTIGENS

HOMEOPATHIC

1 FL OZ (30 ml)